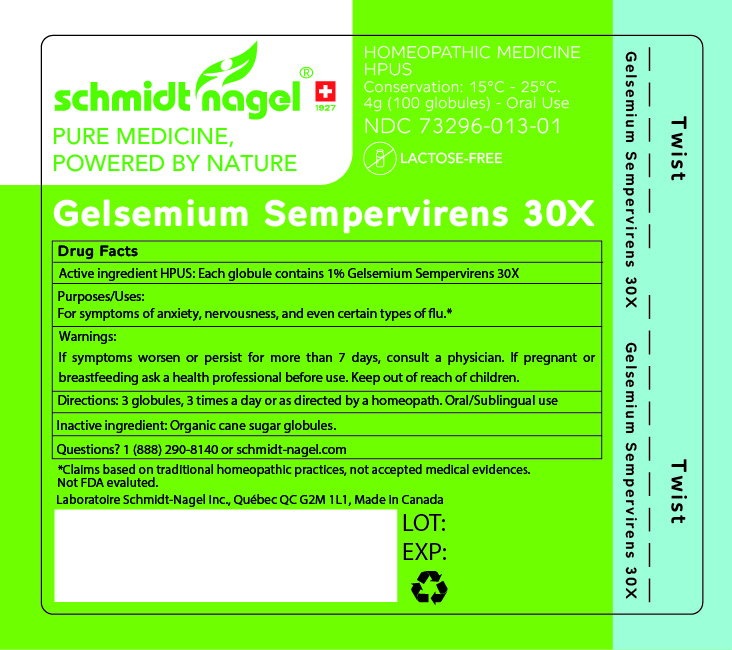 DRUG LABEL: Gelsemium Sempervirens 30X
NDC: 73296-013 | Form: GLOBULE
Manufacturer: Laboratoire Schmidt-Nagel Inc.
Category: homeopathic | Type: HUMAN OTC DRUG LABEL
Date: 20250520

ACTIVE INGREDIENTS: GELSEMIUM SEMPERVIRENS ROOT 30 [hp_X]/1 g
INACTIVE INGREDIENTS: SUGARCANE

Gelsemium Sempervirens 30X - Granules

ACTIVE INGREDIENT

Active ingredients HPUS: Each globule contains 1% Gelsemium Sempervirens 30X

PURPOSE

For symptoms of anxiety, nervousness, and even certain types of flu*

INDICATIONS AND USAGE

For symptoms of anxiety, nervousness, and even certain types of flu*

WARNINGS

If symptoms worsen or persist for more than 7 days, consult a physician.

PREGNANCY OR BREAST FEEDING

If pregnant or breastfeeding, ask a health professional before use.

Keep out of reach of children.

DOSAGE AND ADMINISTRATION

3 globules 3 times a day or as directed by a homeopath. Oral/Sublingual use.

INACTIVE INGREDIENT

Organic cane sugar globules.

QUESTIONS

1 (888) 290-8140 or schmidt-nagel.com

STORAGE AND HANDLING

Conservation: 15°C - 25°C

OTHER SAFETY INFORMATION

*Claims based on traditional homeopathic practices, not accepted medical evidences. Not FDA evaluated.